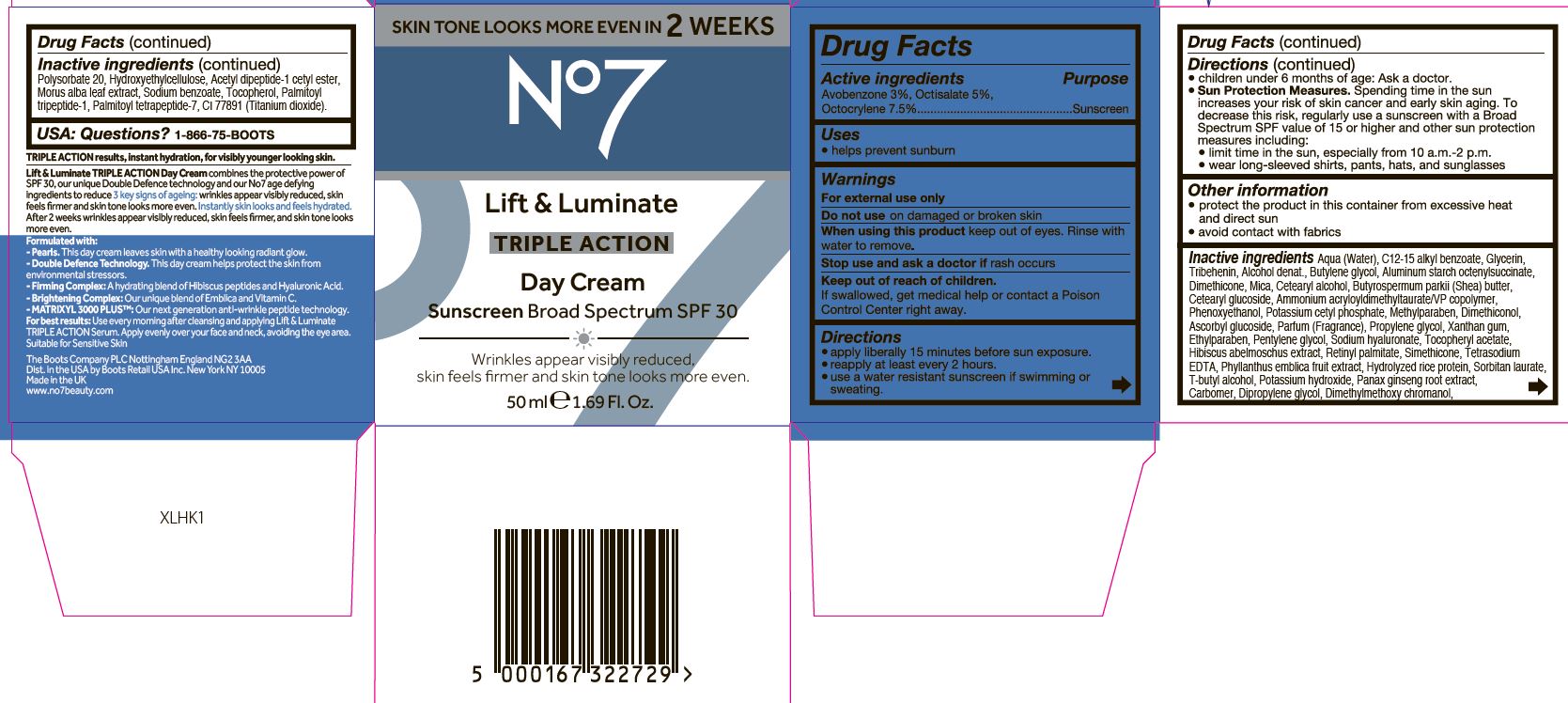 DRUG LABEL: No7 Lift and Luminate Triple Action Day Cream SPF 30
NDC: 61589-9605 | Form: CREAM
Manufacturer: BCM Cosmetique SAS
Category: otc | Type: HUMAN OTC DRUG LABEL
Date: 20250620

ACTIVE INGREDIENTS: AVOBENZONE 1.5 g/50 g; OCTOCRYLENE 3.75 g/50 g; OCTISALATE 2.5 g/50 g
INACTIVE INGREDIENTS: AMMONIUM ACRYLOYLDIMETHYLTAURATE/VP COPOLYMER; PHENOXYETHANOL; CETOSTEARYL ALCOHOL; SHEA BUTTER; BUTYLENE GLYCOL; METHYLPARABEN; DIMETHICONOL (40 CST); ETHYLPARABEN; XANTHAN GUM; SODIUM LAUROYL LACTYLATE; PHYLLANTHUS EMBLICA FRUIT; VITAMIN A PALMITATE; PANAX GINSENG ROOT WATER; ASCORBYL GLUCOSIDE; EDETATE SODIUM; TERT-BUTYL ALCOHOL; PROPYLENE GLYCOL; POLYSORBATE 20; CARBOMER 940; DIPROPYLENE GLYCOL; DIMETHYLMETHOXY CHROMANOL; POTASSIUM HYDROXIDE; N-ACETYL DIPEPTIDE-1; TOCOPHEROL; MORUS ALBA LEAF; SODIUM BENZOATE; TITANIUM DIOXIDE; PALMITOYL TETRAPEPTIDE-7; PALMITOYL TRIPEPTIDE-1; WATER; GLYCERIN; ALUMINUM STARCH OCTENYLSUCCINATE; DIMETHICONE; MICA; ALKYL (C12-15) BENZOATE; CETEARYL GLUCOSIDE; TRIBEHENIN; PENTYLENE GLYCOL

No7 Lift and Luminate Triple Action Day Cream Sunscreen Broad Spectrum SPF 30

Carton Active Ingredients Section

Active ingredients

Avobenzone 3%, Octisalate 5%, Octocrylene 7.5%

Purpose

Sunscreen

Uses

- helps prevent sunburn

Warnings

For external use only

Do not use on damaged or broken skin

When using this product keep out of eyes. Rinse with water to remove

Ask a doctor

Stop use and ask a doctor if rash occurs

Keep out of reach of children

If swallowed, get medical help or contact a Poison Control Center right away.

Directions

- apply liberally 15 minutes before sun exposure.

- reapply at least every 2 hours.

- use a water resistant sunscreen if swimming or sweating.

- children under 6 months of age: Ask a doctor.

- Sun Protection Measures. Spending time in the sun increases your risk of skin cancer and early skin aging. To decrease this risk, regularly use a sunscreen with a Broad Spectrum SPF value of 15 or higher and other sun protection measures including:

- limit time in the sun, especially from 10 a.m.-2 p.m.

- wear long-sleeved shirts, pants, hats and sunglasses

Storage

Other information

- protect the product in this container from excessive heat and direct sun

- avoid contact with fabrics

Inactive ingredients

Aqua (Water), C12-15 alkyl benzoate, Glycerin, Tribehenin, Alcohol denat., Butylene glycol, Aluminum starch octenylsuccinate, Dimethicone, Mica, Catereayl alcohol, Butyrospermum parkii (Shea) butter, Cetearyl glucoside, Ammonium acryloyldimethyltaurate/VP copolymer, Phenoxyethanol, Potassium cetyl phosphate, Methyl paraben, Dimethiconol, Ascorbyl glucoside, Parfum (Fragrance), Propylene glycol, Xanthan gum, Ethylparaben, Pentylene glycol, Sodium hyaluronate, Tocopheryl acetate, Hubiscus abelmoschus extract, Retinyl palmitate, Simethicone, Phyllanthus emblica fruit extract, Hydrolyzed rice protein, Tetrasodium EDTA, Sorbitan laurate, T-butyl alcohol, Potassium hydroxide, Carbomer, Panax ginseng root extract, Dipropylene glycol, Dimethylmethoxy chromanol, Polysorbate 20, Hydroxyethylcellulose, Acetyl dipeptide-1 cetyl ester, Morus alba leaf extract, Sodium benzoate, Tocopherol, Palmitoyl tripeptide-1, Palmitoyl tetrapeptide-7, CI77891 (Titanium dioxide).

Questions

USA: Questions? 1-866-75-BOOTS

The Boots Company PLC Nottingham England NG2 3AA

Boots Retail Ireland Dublin 12 Ireland

Dist. in the USA by Boots Retail USA Inc. New York NY 10005

Made in the UK

www.no7beauty.com

Description

SKIN TONE LOOKS MORE EVEN IN 2 WEEKS

No7 Lift & Luminate TRIPLE ACTION Day Cream Sunscreen Broad Spectrum SPF 30

Wrinkles appear visibly reduced, skin feels firmer and skin tone looks more even.

50 ml e 1.69 US Fl. Oz.

TRIPLE ACTION results, instant hydration, for visibly younger looking skin.

Lift & Luminate TRIPLE ACTION Day Cream combines the protective power of SPF 30, our unique Double Defence technology and our No7 age defying ingredients to reduce 3 key signs of ageing: wrinkles appear visibly reduced, skin feels firmer and skin tone looks more even. Instantly skin looks and feels hydrated. After 2 weeks wrinkles appear visibly reduced, skin feels firmer, and skin tone looks more even.

Formulated with:

- Pearls. This day cream leaves skin with a healthy looking radiant glow.

- Double Defence Technology. This day cream helps protect the skin from environmental stressors.

- Firming Complex: A hydrating blend of hibiscus peptides and Hyaluronic Acid.

- Brightening Complex: Our unique blend of Emblica and Vitamin C.

- MATRIXYL 3000 PLUS: Our next generation anti-wrinkle peptide technology.

For best results: Use every morning after cleansing and applying Lift & Luminate TRIPLE ACTION Serum. Apply evenly over your face and neck, avoiding the eye area.

Suitable for Sensitive Skin

Dosage

Topical apply liberally 15 minutes before sun exposure

Warnings

For external use only

Do not use on damaged or broken skin

When using this product keep out of eyes

Rinse with water to remove

Stop use and ask a doctor if rash occurs

Keep out of reach of children

If swallowed, get medical help or contact a poison control center right away.

Carton